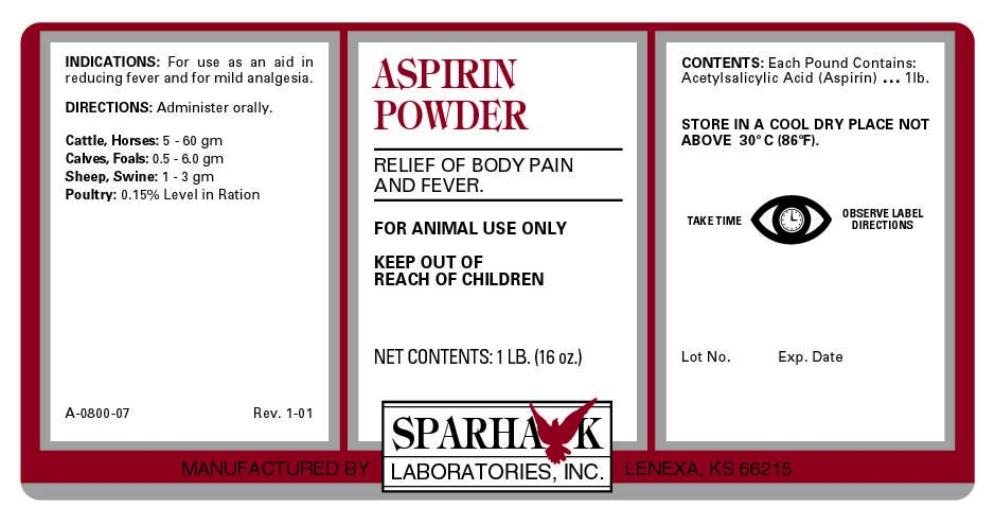 DRUG LABEL: ASPIRIN
NDC: 58005-080 | Form: POWDER
Manufacturer: Sparhawk Laboratories, Inc.
Category: animal | Type: OTC ANIMAL DRUG LABEL
Date: 20251223

ACTIVE INGREDIENTS: ASPIRIN 454 g/454 g

ASPIRIN POWDER RELIEF OF BODY PAIN AND FEVER

INDICATIONS

For use as an aid in reducing fever and for mild analgesia.

DIRECTIONS

Administer orally

Cattle, Horses: 5 - 60 gm
Calves, Foals: 0.5 - 6.0 gm
Sheep, Swine: 1 - 3 gm
Poultry: 0.15% Level in Ration

CONTENTS

Each Pound Contains: Acetylsalicylic Acid (Aspirin) ...... 1 lb.

STORAGE AND HANDLING

STORE IN A COOL DRY PLACE NOT ABOVE 30oC (86oF).
TAKE TIME OBSERVE LABEL DIRECTIONS

PACKAGE LABEL

FOR ANIMAL USE ONLY

KEEP OUT OF REACH OF CHILDREN

Rev. 1-01